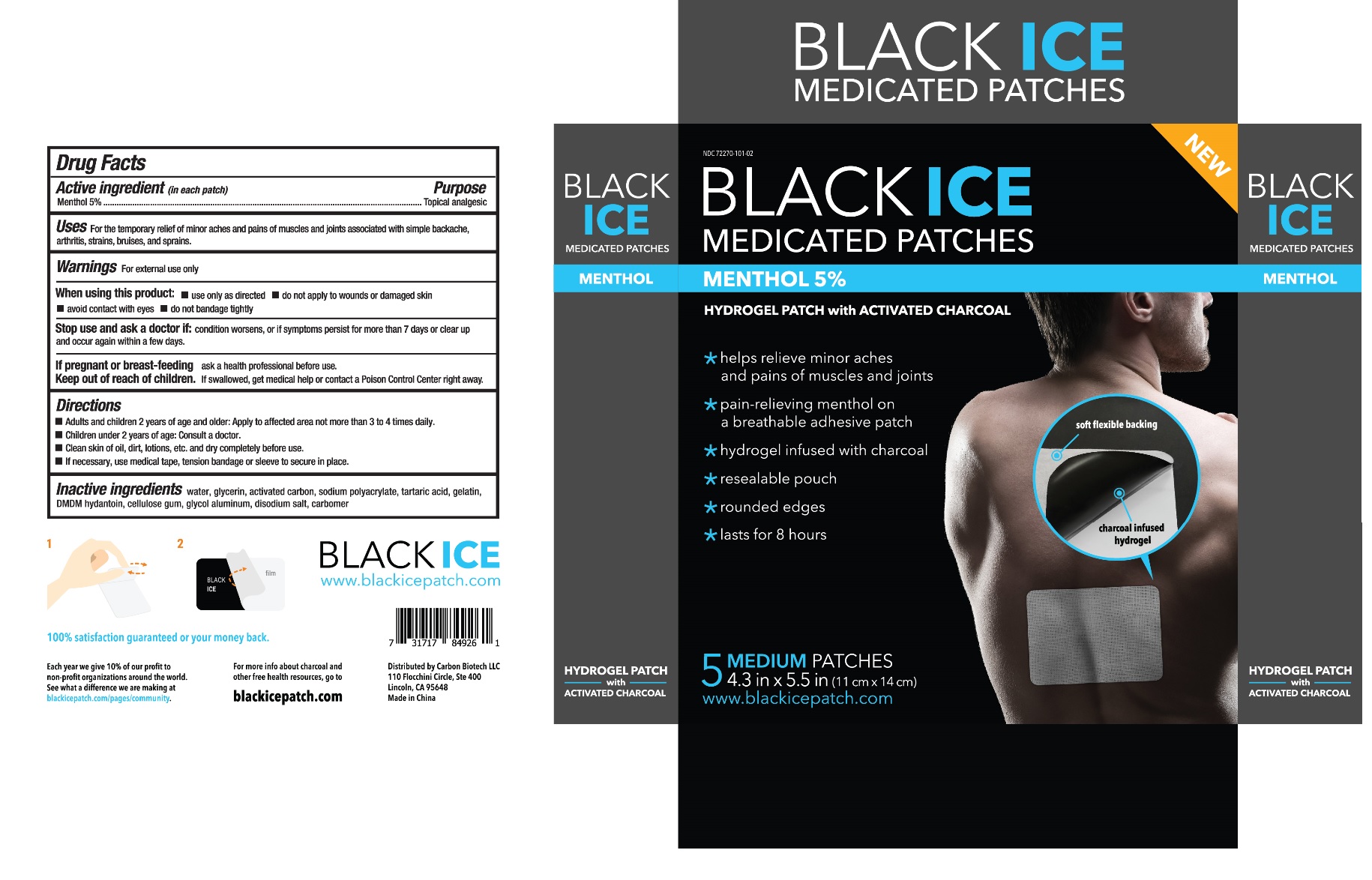 DRUG LABEL: BLACK ICE MEDICATED PATCHES
NDC: 72411-101 | Form: PATCH
Manufacturer: Carbon Biotech Llc
Category: otc | Type: HUMAN OTC DRUG LABEL
Date: 20191217

ACTIVE INGREDIENTS: MENTHOL, UNSPECIFIED FORM 0.348 g/1 1
INACTIVE INGREDIENTS: WATER; GLYCERIN; ACTIVATED CHARCOAL; SODIUM POLYACRYLATE (2500000 MW); TARTARIC ACID; GELATIN, UNSPECIFIED; DMDM HYDANTOIN; CARBOXYMETHYLCELLULOSE SODIUM, UNSPECIFIED FORM; DIHYDROXYALUMINUM AMINOACETATE ANHYDROUS; EDETATE DISODIUM; CARBOMER HOMOPOLYMER, UNSPECIFIED TYPE

BLACK ICE MEDICATED PATCHES

Active ingredient (in each patch)

Menthol 5%

Purpose

Topical analgesic

Uses

For the temporary relief of minor aches and pains of muscles and joints associated with simple backache, arthritis, strains, bruises, and sprains.

Warnings

For external use only

When using this product: • use only as directed • do not apply to wounds or damaged skin • avoid contact with eyes • do not bandage tightly

Stop use and ask a doctor if: condition worsens, or if symptoms persist for more than 7 days or clear up and occur again within a few days.

If pregnant or breast-feeding ask a health professional before use.

Keep out of reach of children. If swallowed, get medical help or contact a Poison Control Center right away.

Directions

- Adults and children 2 years of age and older: Apply to affected area not more than 3 to 4 times daily.
- Children under 2 years of age: Consult a doctor.
- Clean skin of oil, dirt, lotions, etc. and dry completely before use.
- If necessary, use medical tape, tension bandage or sleeve to secure in place.

Inactive ingredients

water, glycerin, activated carbon, sodium polyacrylate, tartaric acid, gelatin, DMDM hydantoin, cellulose gum, glycol aluminum, disodium salt, carbomer

HYDROGEL PATCH with ACTIVATED CHARCOAL

* helps relieve minor aches and pains of muscles and joints

* pain-relieving menthol on a breathable adhesive patch

* hydrogel infused with charcoal for smoother skin

* resealable pouch

* rounded edges

* lasts for 8 hours

100% satisfaction guaranteed or your money back.

For more info about charcoal and other free health resources, go to blackicepatch.com

Distributed by Carbon Biotech LLC

110 Flocchini Circle, Ste 400

Lincoln, CA 95648

Made in China